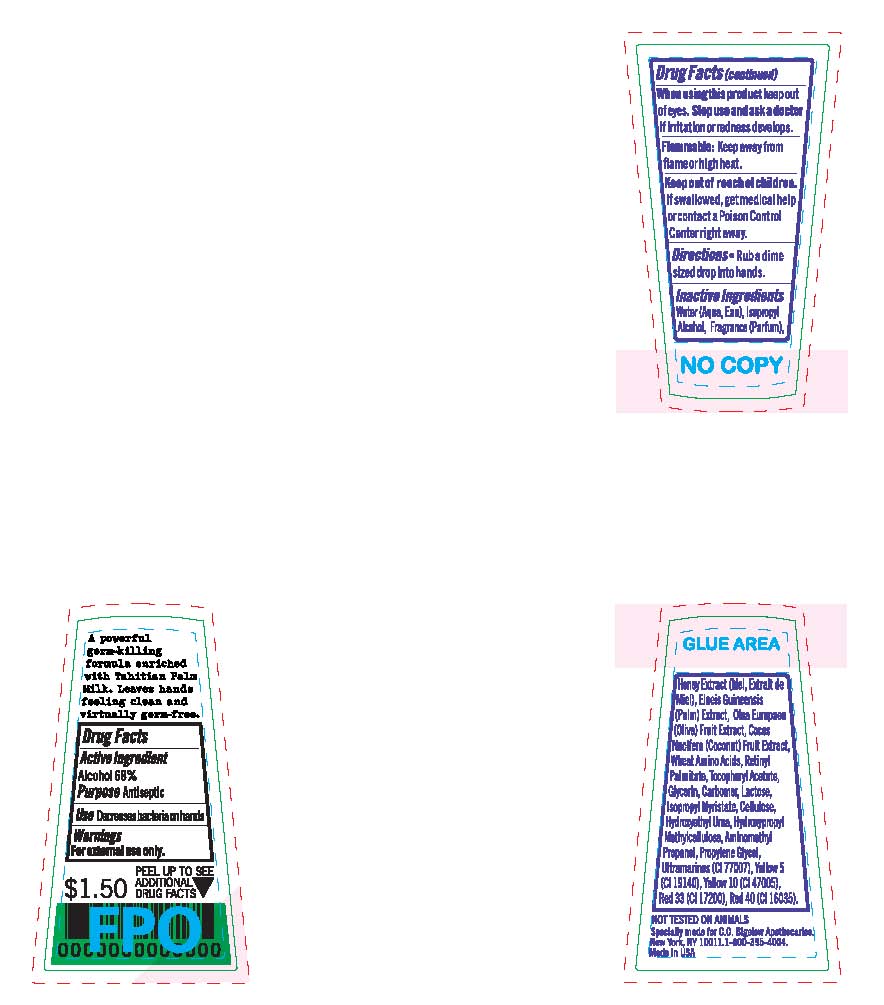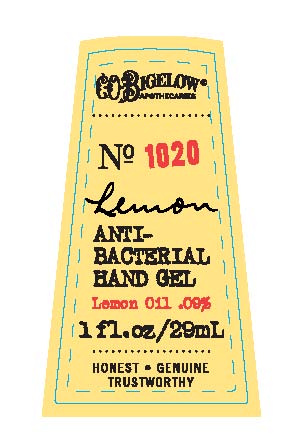 DRUG LABEL: Anti-Bacterial Hand
NDC: 62670-4078 | Form: GEL
Manufacturer: Bath & Body Works, Inc.
Category: otc | Type: HUMAN OTC DRUG LABEL
Date: 20110728

ACTIVE INGREDIENTS: ALCOHOL 68 mL/100 mL

DRUG FACTS

ACTIVE INGREDIENT

Alcohol 68%

PURPOSE

Antiseptic

USE

Decrease bacteria on hands.

WARNINGS

For external use only.

When using this product avoid contact with eyes. If contact occurs, rinse thoroughly with water. Stop use and ask a doctor if irritation and redness develop or increase.

FLAMMABLE

Keep away from flame or high heat.

KEEP OUT OF THE REACH OF CHILDREN

If swallowed, get medical help or contact a Poison Control Center immediately.

DIRECTIONS

- Rub a dime sized drop into hands.

INACTIVE INGREDIENTS

Water (Aqua, Eau), Isopropyl Alcohol, Fragrance (Parfum), Honey Extract (Mel, Extrait de Miel), Elaeis Guineensis (Palm) Extract, Olea Europaea (Olive) Fruit Extract, Cocos Nucifera (Coconut) Fruit Extract, Wheat Amino Acids, Retinyl Palmitate, Tocopheryl Acetate, Glycerin, Carbomer, Lactose, Isopropyl Myristate, Cellulose, Hydroxyethyl Urea, Hydroxypropyl Methylcellulose, Aminomethyl Propanol, Propylene Glycol, Ultramarines (CI 77007), Yellow 5 (CI 19140), Yellow 10 (CI 47005), Red 33 (CI 17200), Red 40 (CI 16035).

COMPANY INFORMATION

Bath & Body Works, Distr.
Reynoldsburg, Ohio 43068
1-800-395-1001
www.bathandbodyworks.com